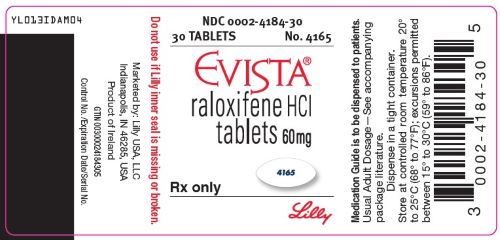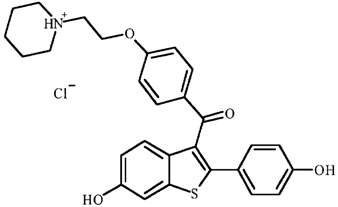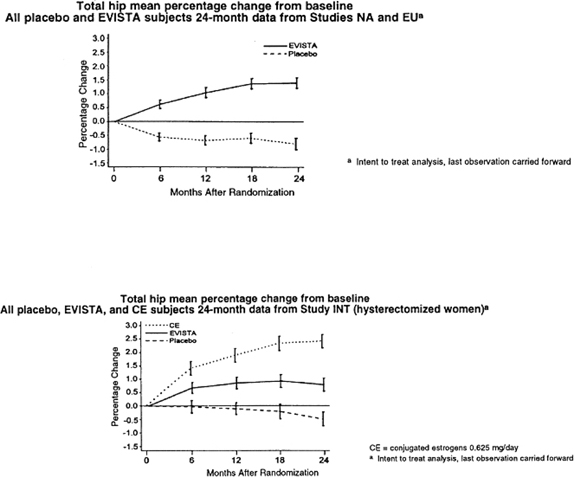 DRUG LABEL: Evista
NDC: 0002-4184 | Form: TABLET
Manufacturer: Eli Lilly and Company
Category: prescription | Type: HUMAN PRESCRIPTION DRUG LABEL
Date: 20250722

ACTIVE INGREDIENTS: Raloxifene hydrochloride 60 mg/1 1
INACTIVE INGREDIENTS: Povidone, Unspecified; Polysorbate 80; Anhydrous lactose; Lactose monohydrate; Crospovidone, Unspecified; Magnesium stearate; Hypromellose, Unspecified; Titanium dioxide; Polyethylene glycol 400; Carnauba Wax; Propylene glycol; Indigotindisulfonate Sodium; Butyl alcohol; Isopropyl alcohol

HIGHLIGHTS OF PRESCRIBING INFORMATION

These highlights do not include all the information needed to use EVISTA safely and effectively. See full prescribing information for EVISTA.
EVISTA (raloxifene hydrochloride) Tablet for Oral Use
Initial U.S. Approval: 1997

WARNING: INCREASED RISK OF VENOUS THROMBOEMBOLISM AND DEATH FROM STROKE

See full prescribing information for complete boxed warning.

- Increased risk of deep vein thrombosis and pulmonary embolism have been reported with EVISTA (5.1). Women with active or past history of venous thromboembolism should not take EVISTA (4.1).
- Increased risk of death due to stroke occurred in a trial in postmenopausal women with documented coronary heart disease or at increased risk for major coronary events. Consider risk-benefit balance in women at risk for stroke (5.2, 14.5).

RECENT MAJOR CHANGES

None

1 INDICATIONS AND USAGE

EVISTA® is an estrogen agonist/antagonist indicated for:

- Treatment and prevention of osteoporosis in postmenopausal women. (1.1)
- Reduction in risk of invasive breast cancer in postmenopausal women with osteoporosis. (1.2)
- Reduction in risk of invasive breast cancer in postmenopausal women at high risk for invasive breast cancer. (1.3)

Important Limitations: EVISTA is not indicated for the treatment of invasive breast cancer, reduction of the risk of recurrence of breast cancer, or reduction of risk of noninvasive breast cancer. (1.3)

2 DOSAGE AND ADMINISTRATION

60 mg tablet orally once daily. (2.1)

3 DOSAGE FORMS AND STRENGTHS

Tablets (not scored): 60 mg (3)

4 CONTRAINDICATIONS

- Active or past history of venous thromboembolism, including deep vein thrombosis, pulmonary embolism, and retinal vein thrombosis. (4.1)
- Pregnancy. (4.2, 8.1)

5 WARNINGS AND PRECAUTIONS

- Venous Thromboembolism: Increased risk of deep vein thrombosis, pulmonary embolism, and retinal vein thrombosis. Discontinue use 72 hours prior to and during prolonged immobilization. (5.1, 6.1)
- Death Due to Stroke: Increased risk of death due to stroke occurred in a trial in postmenopausal women with documented coronary heart disease or at increased risk for major coronary events. No increased risk of stroke was seen in this trial. Consider risk-benefit balance in women at risk for stroke. (5.2, 14.5)
- Cardiovascular Disease: EVISTA should not be used for the primary or secondary prevention of cardiovascular disease. (5.3, 14.5)
- Premenopausal Women: Use is not recommended. (5.4)
- Hepatic Impairment: Use with caution. (5.5)
- Concomitant Use with Systemic Estrogens: Not recommended. (5.6)
- Hypertriglyceridemia: If previous treatment with estrogen resulted in hypertriglyceridemia, monitor serum triglycerides. (5.7)

6 ADVERSE REACTIONS

Adverse reactions (>2% and more common than with placebo) include: hot flashes, leg cramps, peripheral edema, flu syndrome, arthralgia, sweating. (6.1)

To report SUSPECTED ADVERSE REACTIONS, contact Eli Lilly and Company at 1-800-545-5979 or FDA at 1-800-FDA-1088 or www.fda.gov/medwatch

7 DRUG INTERACTIONS

- Cholestyramine: Use with EVISTA is not recommended. Reduces the absorption and enterohepatic cycling of raloxifene. (7.1, 12.3)
- Warfarin: Monitor prothrombin time when starting or stopping EVISTA. (7.2, 12.3)
- Highly Protein-Bound Drugs: Use with EVISTA with caution. Highly protein-bound drugs include diazepam, diazoxide, and lidocaine. EVISTA is more than 95% bound to plasma proteins. (7.3, 12.3)

8 USE IN SPECIFIC POPULATIONS

- Pediatric Use: Safety and effectiveness not established. (8.4)

FULL PRESCRIBING INFORMATION

WARNING: INCREASED RISK OF VENOUS THROMBOEMBOLISM AND DEATH FROM STROKE

- Increased risk of deep vein thrombosis and pulmonary embolism have been reported with EVISTA [see Warnings and Precautions (5.1)]. Women with active or past history of venous thromboembolism should not take EVISTA [see Contraindications (4.1)].
- Increased risk of death due to stroke occurred in a trial in postmenopausal women with documented coronary heart disease or at increased risk for major coronary events. Consider risk-benefit balance in women at risk for stroke [see Warnings and Precautions (5.2) and Clinical Studies (14.5)].

1 INDICATIONS AND USAGE

1.1 Treatment and Prevention of Osteoporosis in Postmenopausal Women

EVISTA is indicated for the treatment and prevention of osteoporosis in postmenopausal women [see Clinical Studies (14.1, 14.2)].

1.2 Reduction in the Risk of Invasive Breast Cancer in Postmenopausal Women with Osteoporosis

EVISTA is indicated for the reduction in risk of invasive breast cancer in postmenopausal women with osteoporosis [see Clinical Studies (14.3)].

1.3 Reduction in the Risk of Invasive Breast Cancer in Postmenopausal Women at High Risk of Invasive Breast Cancer

EVISTA is indicated for the reduction in risk of invasive breast cancer in postmenopausal women at high risk of invasive breast cancer [see Clinical Studies (14.4)].

The effect in the reduction in the incidence of breast cancer was shown in a study of postmenopausal women at high risk for breast cancer with a 5-year planned duration with a median follow-up of 4.3 years [see Clinical Studies (14.4)]. Twenty-seven percent of the participants received drug for 5 years. The long-term effects and the recommended length of treatment are not known.

High risk of breast cancer is defined as at least one breast biopsy showing lobular carcinoma in situ (LCIS) or atypical hyperplasia, one or more first-degree relatives with breast cancer, or a 5-year predicted risk of breast cancer ≥1.66% (based on the modified Gail model). Among the factors included in the modified Gail model are the following: current age, number of first-degree relatives with breast cancer, number of breast biopsies, age at menarche, nulliparity or age of first live birth. Healthcare professionals can obtain a Gail Model Risk Assessment Tool by dialing 1-800-545-5979. Currently, no single clinical finding or test result can quantify risk of breast cancer with certainty.

After an assessment of the risk of developing breast cancer, the decision regarding therapy with EVISTA should be based upon an individual assessment of the benefits and risks.

EVISTA does not eliminate the risk of breast cancer. Patients should have breast exams and mammograms before starting EVISTA and should continue regular breast exams and mammograms in keeping with good medical practice after beginning treatment with EVISTA.

Important Limitations of Use for Breast Cancer Risk Reduction

- There are no data available regarding the effect of EVISTA on invasive breast cancer incidence in women with inherited mutations (BRCA1, BRCA2) to be able to make specific recommendations on the effectiveness of EVISTA.
- EVISTA is not indicated for the treatment of invasive breast cancer or reduction of the risk of recurrence.
- EVISTA is not indicated for the reduction in the risk of noninvasive breast cancer.

2 DOSAGE AND ADMINISTRATION

2.1 Recommended Dosing

The recommended dosage is one 60 mg EVISTA (raloxifene hydrochloride tablets) tablet daily, which may be administered any time of day without regard to meals [see Clinical Pharmacology (12.3)].

For the indications in risk of invasive breast cancer the optimum duration of treatment is not known [see Clinical Studies (14.3, 14.4)].

2.2 Recommendations for Calcium and Vitamin D Supplementation

For either osteoporosis treatment or prevention, supplemental calcium and/or vitamin D should be added to the diet if daily intake is inadequate. Postmenopausal women require an average of 1500 mg/day of elemental calcium. Total daily intake of calcium above 1500 mg has not demonstrated additional bone benefits while daily intake above 2000 mg has been associated with increased risk of adverse effects, including hypercalcemia and kidney stones. The recommended intake of vitamin D is 400-800 IU daily. Patients at increased risk for vitamin D insufficiency (e.g., over the age of 70 years, nursing home bound, or chronically ill) may need additional vitamin D supplements. Patients with gastrointestinal malabsorption syndromes may require higher doses of vitamin D supplementation and measurement of 25-hydroxyvitamin D should be considered.

3 DOSAGE FORMS AND STRENGTHS

60 mg, white, elliptical, film-coated tablets (not scored) imprinted with 4165 on one side in edible blue ink.

4 CONTRAINDICATIONS

4.1 Venous Thromboembolism

EVISTA is contraindicated in women with active or past history of venous thromboembolism (VTE), including deep vein thrombosis, pulmonary embolism, and retinal vein thrombosis [see Warnings and Precautions (5.1)].

4.2 Pregnancy

EVISTA is contraindicated for use in pregnancy, as it may cause fetal harm [see Use in Specific Populations (8.1)].

5 WARNINGS AND PRECAUTIONS

5.1 Venous Thromboembolism

In clinical trials, EVISTA-treated women had an increased risk of venous thromboembolism (deep vein thrombosis and pulmonary embolism). Other venous thromboembolic events also could occur. A less serious event, superficial thrombophlebitis, also has been reported more frequently with EVISTA than with placebo. The greatest risk for deep vein thrombosis and pulmonary embolism occurs during the first 4 months of treatment, and the magnitude of risk appears to be similar to the reported risk associated with use of hormone therapy. Because immobilization increases the risk for venous thromboembolic events independent of therapy, EVISTA should be discontinued at least 72 hours prior to and during prolonged immobilization (e.g., post-surgical recovery, prolonged bed rest), and EVISTA therapy should be resumed only after the patient is fully ambulatory. In addition, women taking EVISTA should be advised to move about periodically during prolonged travel. The risk-benefit balance should be considered in women at risk of thromboembolic disease for other reasons, such as congestive heart failure, superficial thrombophlebitis, and active malignancy [see Contraindications (4.1) and Adverse Reactions (6.1)].

5.2 Death Due to Stroke

In a clinical trial of postmenopausal women with documented coronary heart disease or at increased risk for coronary events, an increased risk of death due to stroke was observed after treatment with EVISTA. During an average follow-up of 5.6 years, 59 (1.2%) EVISTA-treated women died due to a stroke compared to 39 (0.8%) placebo-treated women (22 versus 15 per 10,000 women-years; hazard ratio 1.49; 95% confidence interval, 1.00-2.24; p=0.0499). There was no statistically significant difference between treatment groups in the incidence of stroke (249 in EVISTA [4.9%] versus 224 placebo [4.4%]). EVISTA had no significant effect on all-cause mortality. The risk-benefit balance should be considered in women at risk for stroke, such as prior stroke or transient ischemic attack (TIA), atrial fibrillation, hypertension, or cigarette smoking [see Clinical Studies (14.5)].

5.3 Cardiovascular Disease

EVISTA should not be used for the primary or secondary prevention of cardiovascular disease. In a clinical trial of postmenopausal women with documented coronary heart disease or at increased risk for coronary events, no cardiovascular benefit was demonstrated after treatment with raloxifene for 5 years [see Clinical Studies (14.5)].

5.4 Premenopausal Use

There is no indication for premenopausal use of EVISTA. Safety of EVISTA in premenopausal women has not been established and its use is not recommended. Additionally, there is concern regarding inadvertent drug exposure in pregnancy in women of reproductive potential who become pregnant, due to risk of fetal harm [see Use in Specific Populations (8.1)].

5.5 Hepatic Impairment

EVISTA should be used with caution in patients with hepatic impairment. Safety and efficacy have not been established in patients with hepatic impairment [see Clinical Pharmacology (12.3)].

5.6 Concomitant Estrogen Therapy

The safety of concomitant use of EVISTA with systemic estrogens has not been established and its use is not recommended.

5.7 History of Hypertriglyceridemia when Treated with Estrogens

Limited clinical data suggest that some women with a history of marked hypertriglyceridemia (>5.6 mmol/L or >500 mg/dL) in response to treatment with oral estrogen or estrogen plus progestin may develop increased levels of triglycerides when treated with EVISTA. Women with this medical history should have serum triglycerides monitored when taking EVISTA.

5.8 Renal Impairment

EVISTA should be used with caution in patients with moderate or severe renal impairment. Safety and efficacy have not been established in patients with moderate or severe renal impairment [see Clinical Pharmacology (12.3)].

5.9 History of Breast Cancer

EVISTA has not been adequately studied in women with a prior history of breast cancer.

5.10 Use in Men

There is no indication for the use of EVISTA in men. EVISTA has not been adequately studied in men and its use is not recommended.

5.11 Unexplained Uterine Bleeding

Any unexplained uterine bleeding should be investigated as clinically indicated. EVISTA-treated and placebo-treated groups had similar incidences of endometrial proliferation [see Clinical Studies (14.1, 14.2)].

5.12 Breast Abnormalities

Any unexplained breast abnormality occurring during EVISTA therapy should be investigated. EVISTA does not eliminate the risk of breast cancer [see Clinical Studies (14.4)].

6 ADVERSE REACTIONS

6.1 Clinical Trials Experience

Because clinical studies are conducted under widely varying conditions, adverse reaction rates observed in the clinical trials of a drug cannot be directly compared to rates in the clinical trials of another drug and may not reflect the rates observed in practice.

The data described below reflect exposure to EVISTA in 8429 patients who were enrolled in placebo-controlled trials, including 6666 exposed for 1 year and 5685 for at least 3 years.

Osteoporosis Treatment Clinical Trial (MORE) — The safety of raloxifene in the treatment of osteoporosis was assessed in a large (7705 patients) multinational, placebo-controlled trial. Duration of treatment was 36 months, and 5129 postmenopausal women were exposed to raloxifene hydrochloride (2557 received 60 mg/day, and 2572 received 120 mg/day). The incidence of all-cause mortality was similar among groups: 23 (0.9%) placebo, 13 (0.5%) EVISTA-treated (raloxifene HCl 60 mg), and 28 (1.1%) raloxifene HCl 120 mg women died. Therapy was discontinued due to an adverse reaction in 10.9% of EVISTA-treated women and 8.8% of placebo-treated women.

Venous Thromboembolism: The most serious adverse reaction related to EVISTA was VTE (deep venous thrombosis, pulmonary embolism, and retinal vein thrombosis). During an average of study-drug exposure of 2.6 years, VTE occurred in about 1 out of 100 patients treated with EVISTA. Twenty-six EVISTA-treated women had a VTE compared to 11 placebo-treated women, the hazard ratio was 2.4 (95% confidence interval, 1.2, 4.5), and the highest VTE risk was during the initial months of treatment.

Common adverse reactions considered to be related to EVISTA therapy were hot flashes and leg cramps. Hot flashes occurred in about one in 10 patients on EVISTA and were most commonly reported during the first 6 months of treatment and were not different from placebo thereafter. Leg cramps occurred in about one in 14 patients on EVISTA.

Placebo-Controlled Osteoporosis Prevention Clinical Trials — The safety of raloxifene has been assessed primarily in 12 Phase 2 and Phase 3 studies with placebo, estrogen, and estrogen-progestin therapy control groups. The duration of treatment ranged from 2 to 30 months, and 2036 women were exposed to raloxifene HCl (371 patients received 10 to 50 mg/day, 828 received 60 mg/day, and 837 received from 120 to 600 mg/day).

Therapy was discontinued due to an adverse reaction in 11.4% of 581 EVISTA-treated women and 12.2% of 584 placebo-treated women. Discontinuation rates due to hot flashes did not differ significantly between EVISTA and placebo groups (1.7% and 2.2%, respectively).

Common adverse reactions considered to be drug-related were hot flashes and leg cramps. Hot flashes occurred in about one in four patients on EVISTA versus about one in six on placebo. The first occurrence of hot flashes was most commonly reported during the first 6 months of treatment.

Table 1 lists adverse reactions occurring in either the osteoporosis treatment or in five prevention placebo-controlled clinical trials at a frequency ≥2.0% in either group and in more EVISTA-treated women than in placebo-treated women. Adverse reactions are shown without attribution of causality. The majority of adverse reactions occurring during the studies were mild and generally did not require discontinuation of therapy.

Table 1: Adverse Reactions Occurring in Placebo-Controlled Osteoporosis Clinical Trials at a Frequency ≥2.0% and in More EVISTA-Treated (60 mg Once Daily) Women than Placebo-Treated Womena
 | Treatment |  | Prevention
 | EVISTA (N=2557) % | Placebo (N=2576) % | EVISTA (N=581) % | Placebo (N=584) %
Body as a Whole
Infection | A | A | 15.1 | 14.6
Flu Syndrome | 13.5 | 11.4 | 14.6 | 13.5
Headache | 9.2 | 8.5 | A | A
Leg Cramps | 7.0 | 3.7 | 5.9 | 1.9
Chest Pain | A | A | 4.0 | 3.6
Fever | 3.9 | 3.8 | 3.1 | 2.6
Cardiovascular System
Hot Flashes | 9.7 | 6.4 | 24.6 | 18.3
Migraine | A | A | 2.4 | 2.1
Syncope | 2.3 | 2.1 | B | B
Varicose Vein | 2.2 | 1.5 | A | A
Digestive System
Nausea | 8.3 | 7.8 | 8.8 | 8.6
Diarrhea | 7.2 | 6.9 | A | A
Dyspepsia | A | A | 5.9 | 5.8
Vomiting | 4.8 | 4.3 | 3.4 | 3.3
Flatulence | A | A | 3.1 | 2.4
Gastrointestinal Disorder | A | A | 3.3 | 2.1
Gastroenteritis | B | B | 2.6 | 2.1
Metabolic and Nutritional
Weight Gain | A | A | 8.8 | 6.8
Peripheral Edema | 5.2 | 4.4 | 3.3 | 1.9
Musculoskeletal System
Arthralgia | 15.5 | 14.0 | 10.7 | 10.1
Myalgia | A | A | 7.7 | 6.2
Arthritis | A | A | 4.0 | 3.6
Tendon Disorder | 3.6 | 3.1 | A | A
Nervous System
Depression | A | A | 6.4 | 6.0
Insomnia | A | A | 5.5 | 4.3
Vertigo | 4.1 | 3.7 | A | A
Neuralgia | 2.4 | 1.9 | B | B
Hypesthesia | 2.1 | 2.0 | B | B
Respiratory System
Sinusitis | 7.9 | 7.5 | 10.3 | 6.5
Rhinitis | 10.2 | 10.1 | A | A
Bronchitis | 9.5 | 8.6 | A | A
Pharyngitis | 5.3 | 5.1 | 7.6 | 7.2
Cough Increased | 9.3 | 9.2 | 6.0 | 5.7
Pneumonia | A | A | 2.6 | 1.5
Laryngitis | B | B | 2.2 | 1.4
Skin and Appendages
Rash | A | A | 5.5 | 3.8
Sweating | 2.5 | 2.0 | 3.1 | 1.7
Special Senses
Conjunctivitis | 2.2 | 1.7 | A | A
Urogenital System
Vaginitis | A | A | 4.3 | 3.6
Urinary Tract Infection | A | A | 4.0 | 3.9
Cystitis | 4.6 | 4.5 | 3.3 | 3.1
Leukorrhea | A | A | 3.3 | 1.7
Uterine Disorderb, c | 3.3 | 2.3 | A | A
Endometrial Disorderb | B | B | 3.1 | 1.9
Vaginal Hemorrhage | 2.5 | 2.4 | A | A
Urinary Tract Disorder | 2.5 | 2.1 | A | A
a A: Placebo incidence greater than or equal to EVISTA incidence; B: Less than 2% incidence and more frequent with EVISTA.
b Includes only patients with an intact uterus: Prevention Trials: EVISTA, n=354, Placebo, n=364; Treatment Trial: EVISTA, n=1948, Placebo, n=1999.
c Actual terms most frequently referred to endometrial fluid.

Comparison of EVISTA and Hormone Therapy — EVISTA was compared with estrogen-progestin therapy in three clinical trials for prevention of osteoporosis. Table 2 shows adverse reactions occurring more frequently in one treatment group and at an incidence ≥2.0% in any group. Adverse reactions are shown without attribution of causality.

Table 2: Adverse Reactions Reported in the Clinical Trials for Osteoporosis Prevention with EVISTA (60 mg Once Daily) and Continuous Combined or Cyclic Estrogen Plus Progestin (Hormone Therapy) at an Incidence ≥2.0% in any Treatment Groupa
 | EVISTA (N=317) % | Hormone Therapy-Continuous Combinedb (N=96) % | Hormone Therapy-Cyclicc (N=219) %
Urogenital
Breast Pain | 4.4 | 37.5 | 29.7
Vaginal Bleedingd | 6.2 | 64.2 | 88.5
Digestive
Flatulence | 1.6 | 12.5 | 6.4
Cardiovascular
Hot Flashes | 28.7 | 3.1 | 5.9
Body as a Whole
Infection | 11.0 | 0 | 6.8
Abdominal Pain | 6.6 | 10.4 | 18.7
Chest Pain | 2.8 | 0 | 0.5
a These data are from both blinded and open-label studies.
b Continuous Combined Hormone Therapy = 0.625 mg conjugated estrogens plus 2.5 mg medroxyprogesterone acetate.
c Cyclic Hormone Therapy = 0.625 mg conjugated estrogens for 28 days with concomitant 5 mg medroxyprogesterone acetate or 0.15 mg norgestrel on Days 1 through 14 or 17 through 28.
d Includes only patients with an intact uterus: EVISTA, n=290; Hormone Therapy-Continuous Combined, n=67; Hormone Therapy-Cyclic, n=217.

Breast Pain — Across all placebo-controlled trials, EVISTA was indistinguishable from placebo with regard to frequency and severity of breast pain and tenderness. EVISTA was associated with less breast pain and tenderness than reported by women receiving estrogens with or without added progestin.

Gynecologic Cancers — EVISTA-treated and placebo-treated groups had similar incidences of endometrial cancer and ovarian cancer.

Placebo-Controlled Trial of Postmenopausal Women at Increased Risk for Major Coronary Events (RUTH) — The safety of EVISTA (60 mg once daily) was assessed in a placebo-controlled multinational trial of 10,101 postmenopausal women (age range 55-92) with documented coronary heart disease (CHD) or multiple CHD risk factors. Median study drug exposure was 5.1 years for both treatment groups [see Clinical Studies (14.3)]. Therapy was discontinued due to an adverse reaction in 25% of 5044 EVISTA-treated women and 24% of 5057 placebo-treated women. The incidence per year of all-cause mortality was similar between the raloxifene (2.07%) and placebo (2.25%) groups.

Adverse reactions reported more frequently in EVISTA-treated women than in placebo-treated women included peripheral edema (14.1% raloxifene versus 11.7% placebo), muscle spasms/leg cramps (12.1% raloxifene versus 8.3% placebo), hot flashes (7.8% raloxifene versus 4.7% placebo), venous thromboembolic events (2.0% raloxifene versus 1.4% placebo), and cholelithiasis (3.3% raloxifene versus 2.6% placebo) [see Clinical Studies (14.3, 14.5)].

Tamoxifen-Controlled Trial of Postmenopausal Women at Increased Risk for Invasive Breast Cancer (STAR) — The safety of EVISTA 60 mg/day versus tamoxifen 20 mg/day over 5 years was assessed in 19,747 postmenopausal women (age range 35-83 years) in a randomized, double-blind trial. As of 31 December 2005, the median follow-up was 4.3 years. The safety profile of raloxifene was similar to that in the placebo-controlled raloxifene trials [see Clinical Studies (14.4)].

6.2 Postmarketing Experience

Because these reactions are reported voluntarily from a population of uncertain size, it is not always possible to reliably estimate their frequency or establish a causal relationship to drug exposure.

Adverse reactions reported very rarely since market introduction include retinal vein occlusion, stroke, and death associated with venous thromboembolism (VTE).

7 DRUG INTERACTIONS

7.1 Cholestyramine

Concomitant administration of cholestyramine with EVISTA is not recommended. Although not specifically studied, it is anticipated that other anion exchange resins would have a similar effect. EVISTA should not be co-administered with other anion exchange resins [see Clinical Pharmacology (12.3)].

7.2 Warfarin

If EVISTA is given concomitantly with warfarin or other warfarin derivatives, prothrombin time should be monitored more closely when starting or stopping therapy with EVISTA [see Clinical Pharmacology (12.3)].

7.3 Other Highly Protein-Bound Drugs

EVISTA should be used with caution with certain other highly protein-bound drugs such as diazepam, diazoxide, and lidocaine. Although not examined, EVISTA might affect the protein binding of other drugs. Raloxifene is more than 95% bound to plasma proteins [see Clinical Pharmacology (12.3)].

7.4 Systemic Estrogens

The safety of concomitant use of EVISTA with systemic estrogens has not been established and its use is not recommended.

7.5 Other Concomitant Medications

EVISTA can be concomitantly administered with ampicillin, amoxicillin, antacids, corticosteroids, and digoxin [see Clinical Pharmacology (12.3)].

The concomitant use of EVISTA and lipid-lowering agents has not been studied.

8 USE IN SPECIFIC POPULATIONS

8.1 Pregnancy

Risk Summary

EVISTA is contraindicated for use in pregnant women, and is not indicated for use in females of reproductive potential. Based on mechanism of action, EVISTA may block the important functions that estrogen has during all stages of pregnancy [see Clinical Pharmacology (12.1)]. Limited data with EVISTA use in pregnant women are insufficient to inform any drug associated risks for births defects or miscarriage.

In rabbits and rats dosed during organogenesis or during gestation and lactation, EVISTA produced multiple adverse reproductive and developmental effects, including abortion; fetal anomalies; and delayed or disrupted parturition leading to maternal and neonatal mortality, at doses less than or similar to the maximum recommended human dose (based on human body surface area comparison).

Data

Animal Data

In the developmental and reproductive toxicity studies conducted with EVISTA, numerous adverse effects were observed in multiple animal species. In rabbits dosed during organogenesis, abortion and a low rate of fetal heart anomalies (ventricular septal defects) occurred at doses ≥0.1 mg/kg (≥0.04 times the human dose based on surface area, mg/m^2). In rats dosed during organogenesis, retardation of fetal growth and developmental abnormalities (wavy ribs, kidney cavitation) occurred at doses ≥1 mg/kg (≥0.2 times the human dose based on surface area, mg/m^2). Treatment of rats during gestation and lactation with doses of 0.1 to 10 mg/kg (0.02 to 1.6 times the human dose based on surface area, mg/m^2) produced effects that included delayed and disrupted parturition, decreased neonatal survival and altered physical development, sex- and age-specific reductions in growth and changes in pituitary hormone content, and decreased lymphoid compartment size in offspring. At 10 mg/kg, the disruption of parturition resulted in maternal and progeny morbidity and death. Effects in adult offspring (4 months of age) included uterine hypoplasia and reduced fertility; however, no ovarian or vaginal pathology was observed.

8.2 Lactation

Risk Summary

EVISTA is not indicated for use in females of reproductive potential. There is no information on the presence of raloxifene in human milk, the effects on the breastfed child, or the effects on milk production. However, based on mechanism of action, EVISTA may block the important functions that estrogen has in mammary tissue during lactation [see Clinical Pharmacology (12.1)].

8.4 Pediatric Use

Safety and effectiveness in pediatric patients have not been established.

8.5 Geriatric Use

Of the total number of patients in placebo-controlled clinical studies of EVISTA, 61% were 65 and over, while 15.5% were 75 and over. No overall differences in safety or effectiveness were observed between these subjects and younger subjects, and other reported clinical experience has not identified differences in responses between the elderly and younger patients, but greater sensitivity of some older individuals cannot be ruled out. Based on clinical trials, there is no need for dose adjustment for geriatric patients [see Clinical Pharmacology (12.3)].

8.6 Renal Impairment

EVISTA should be used with caution in patients with moderate or severe renal impairment [see Warnings and Precautions (5.8) and Clinical Pharmacology (12.3)].

8.7 Hepatic Impairment

EVISTA should be used with caution in patients with hepatic impairment [see Warnings and Precautions (5.5) and Clinical Pharmacology (12.3)].

10 OVERDOSAGE

In an 8-week study of 63 postmenopausal women, a dose of raloxifene hydrochloride (HCl) 600 mg/day was safely tolerated. In clinical trials, no raloxifene overdose has been reported.

In postmarketing spontaneous reports, raloxifene overdose has been reported very rarely (less than 1 out of 10,000 [<0.01%] patients treated). The highest overdose has been approximately 1.5 grams. No fatalities associated with raloxifene overdose have been reported. Adverse reactions were reported in approximately half of the adults who took ≥180 mg raloxifene HCl and included leg cramps and dizziness.

Two 18-month-old children each ingested raloxifene HCl 180 mg. In these two children, symptoms reported included ataxia, dizziness, vomiting, rash, diarrhea, tremor, and flushing, as well as elevation in alkaline phosphatase.

There is no specific antidote for raloxifene.

No mortality was seen after a single oral dose in rats or mice at 5000 mg/kg (810 times the human dose for rats and 405 times the human dose for mice based on surface area, mg/m^2) or in monkeys at 1000 mg/kg (80 times the AUC in humans).

11 DESCRIPTION

EVISTA (raloxifene hydrochloride) is an estrogen agonist/antagonist, commonly referred to as a selective estrogen receptor modulator (SERM) that belongs to the benzothiophene class of compounds. The chemical structure is:

The chemical designation is methanone, [6-hydroxy-2-(4-hydroxyphenyl)benzo[b]thien-3-yl]-[4-[2-(1-piperidinyl)ethoxy]phenyl]-, hydrochloride. Raloxifene hydrochloride (HCl) has the empirical formula C28H27NO4S•HCl, which corresponds to a molecular weight of 510.05. Raloxifene HCl is an off-white to pale-yellow solid that is very slightly soluble in water.

EVISTA is supplied in a tablet dosage form for oral administration. Each EVISTA tablet contains 60 mg of raloxifene HCl, which is the molar equivalent of 55.71 mg of free base. Inactive ingredients include anhydrous lactose, carnauba wax, crospovidone, FD&C Blue No. 2 aluminum lake, hypromellose, lactose monohydrate, magnesium stearate, modified pharmaceutical glaze, polyethylene glycol, polysorbate 80, povidone, propylene glycol, and titanium dioxide.

12 CLINICAL PHARMACOLOGY

12.1 Mechanism of Action

Raloxifene is an estrogen agonist/antagonist, commonly referred to as a selective estrogen receptor modulator (SERM). The biological actions of raloxifene are largely mediated through binding to estrogen receptors. This binding results in activation of estrogenic pathways in some tissues (agonism) and blockade of estrogenic pathways in others (antagonism). The agonistic or antagonistic action of raloxifene depends on the extent of recruitment of coactivators and corepressors to estrogen receptor (ER) target gene promoters.

Raloxifene appears to act as an estrogen agonist in bone. It decreases bone resorption and bone turnover, increases bone mineral density (BMD) and decreases fracture incidence. Preclinical data demonstrate that raloxifene is an estrogen antagonist in uterine and breast tissues. These results are consistent with findings in clinical trials, which suggest that EVISTA lacks estrogen-like effects on the uterus and breast tissue.

12.2 Pharmacodynamics

Decreases in estrogen levels after oophorectomy or menopause lead to increases in bone resorption and accelerated bone loss. Bone is initially lost rapidly because the compensatory increase in bone formation is inadequate to offset resorptive losses. In addition to loss of estrogen, this imbalance between resorption and formation may be due to age-related impairment of osteoblasts or their precursors. In some women, these changes will eventually lead to decreased bone mass, osteoporosis, and increased risk for fractures, particularly of the spine, hip, and wrist. Vertebral fractures are the most common type of osteoporotic fracture in postmenopausal women.

In both the osteoporosis treatment and prevention trials, EVISTA therapy resulted in consistent, statistically significant suppression of bone resorption and bone formation, as reflected by changes in serum and urine markers of bone turnover (e.g., bone-specific alkaline phosphatase, osteocalcin, and collagen breakdown products). The suppression of bone turnover markers was evident by 3 months and persisted throughout the 36-month and 24-month observation periods.

In a 31-week, open-label, radiocalcium kinetics study, 33 early postmenopausal women were randomized to treatment with once-daily EVISTA 60 mg, cyclic estrogen/progestin (0.625 mg conjugated estrogens daily with 5 mg medroxyprogesterone acetate daily for the first 2 weeks of each month [hormone therapy]), or no treatment. Treatment with either EVISTA or hormone therapy was associated with reduced bone resorption and a positive shift in calcium balance (-82 mg Ca/day and +60 mg Ca/day, respectively, for EVISTA and -162 mg Ca/day and +91 mg Ca/day, respectively, for hormone therapy).

There were small decreases in serum total calcium, inorganic phosphate, total protein, and albumin, which were generally of lesser magnitude than decreases observed during estrogen or hormone therapy. Platelet count was also decreased slightly and was not different from estrogen therapy.

12.3 Pharmacokinetics

The disposition of raloxifene has been evaluated in more than 3000 postmenopausal women in selected raloxifene osteoporosis treatment and prevention clinical trials, using a population approach. Pharmacokinetic data also were obtained in conventional pharmacology studies in 292 postmenopausal women. Raloxifene exhibits high within-subject variability (approximately 30% coefficient of variation) of most pharmacokinetic parameters. Table 3 summarizes the pharmacokinetic parameters of raloxifene.

Absorption — Raloxifene is absorbed rapidly after oral administration. Approximately 60% of an oral dose is absorbed, but presystemic glucuronide conjugation is extensive. Absolute bioavailability of raloxifene is 2%. The time to reach average maximum plasma concentration and bioavailability are functions of systemic interconversion and enterohepatic cycling of raloxifene and its glucuronide metabolites.

Administration of raloxifene HCl with a standardized, high-fat meal increases the absorption of raloxifene (Cmax 28% and AUC 16%), but does not lead to clinically meaningful changes in systemic exposure. EVISTA can be administered without regard to meals.

Distribution — Following oral administration of single doses ranging from 30 to 150 mg of raloxifene HCl, the apparent volume of distribution is 2348 L/kg and is not dose dependent.

Raloxifene and the monoglucuronide conjugates are highly (95%) bound to plasma proteins. Raloxifene binds to both albumin and α1-acid glycoprotein, but not to sex-steroid binding globulin.

Metabolism — Biotransformation and disposition of raloxifene in humans have been determined following oral administration of ^14C-labeled raloxifene. Raloxifene undergoes extensive first-pass metabolism to the glucuronide conjugates: raloxifene-4′-glucuronide, raloxifene-6-glucuronide, and raloxifene-6, 4′-diglucuronide. No other metabolites have been detected, providing strong evidence that raloxifene is not metabolized by cytochrome P450 pathways. Unconjugated raloxifene comprises less than 1% of the total radiolabeled material in plasma. The terminal log-linear portions of the plasma concentration curves for raloxifene and the glucuronides are generally parallel. This is consistent with interconversion of raloxifene and the glucuronide metabolites.

Following intravenous administration, raloxifene is cleared at a rate approximating hepatic blood flow. Apparent oral clearance is 44.1 L/kg•hr. Raloxifene and its glucuronide conjugates are interconverted by reversible systemic metabolism and enterohepatic cycling, thereby prolonging its plasma elimination half-life to 27.7 hours after oral dosing.

Results from single oral doses of raloxifene predict multiple-dose pharmacokinetics. Following chronic dosing, clearance ranges from 40 to 60 L/kg•hr. Increasing doses of raloxifene HCl (ranging from 30 to 150 mg) result in slightly less than a proportional increase in the area under the plasma time concentration curve (AUC).

Excretion — Raloxifene is primarily excreted in feces, and less than 0.2% is excreted unchanged in urine. Less than 6% of the raloxifene dose is eliminated in urine as glucuronide conjugates.

Table 3: Summary of Raloxifene Pharmacokinetic Parameters in the Healthy Postmenopausal Woman
 | Cmaxa, b (ng/mL)/ (mg/kg) | t1/2 (hr)a | AUC0-∞a, b (ng•hr/mL)/ (mg/kg) | CL/Fa (L/kg•hr) | V/Fa (L/kg)
Single Dose Mean | 0.50 | 27.7 | 27.2 | 44.1 | 2348
CVa (%) | 52 | 10.7 to 273c | 44 | 46 | 52
Multiple Dose Mean | 1.36 | 32.5 | 24.2 | 47.4 | 2853
CVa (%) | 37 | 15.8 to 86.6c | 36 | 41 | 56
a Abbreviations: Cmax = maximum plasma concentration, t1/2 = half-life, AUC = area under the curve, CL = clearance, V = volume of distribution, F = bioavailability, CV = coefficient of variation.
b Data normalized for dose in mg and body weight in kg.
c Range of observed half-life.

Special Populations

Pediatric — The pharmacokinetics of raloxifene has not been evaluated in a pediatric population [see Use in Specific Populations (8.4)].

Geriatric — No differences in raloxifene pharmacokinetics were detected with regard to age (range 42 to 84 years) [see Use in Specific Populations (8.5)].

Gender — Total extent of exposure and oral clearance, normalized for lean body weight, are not significantly different between age-matched female and male volunteers.

Race — Pharmacokinetic differences due to race have been studied in 1712 women, including 97.5% White, 1.0% Asian, 0.7% Hispanic, and 0.5% Black in the osteoporosis treatment trial and in 1053 women, including 93.5% White, 4.3% Hispanic, 1.2% Asian, and 0.5% Black in the osteoporosis prevention trials. There were no discernible differences in raloxifene plasma concentrations among these groups; however, the influence of race cannot be conclusively determined.

Renal Impairment — In the osteoporosis treatment and prevention trials, raloxifene concentrations in women with mild renal impairment are similar to women with normal creatinine clearance. When a single dose of 120 mg raloxifene HCl was administered to 10 renally impaired males [7 moderate impairment (CrCl = 31–50 mL/min); 3 severe impairment (CrCl ≤30 mL/min)] and to 10 healthy males (CrCl >80 mL/min), plasma raloxifene concentrations were 122% (AUC0-∞) higher in renally impaired patients than those of healthy volunteers. Raloxifene should be used with caution in patients with moderate or severe renal impairment [see Warnings and Precautions (5.8) and Use in Specific Populations (8.6)].

Hepatic Impairment — The disposition of raloxifene was compared in 9 patients with mild (Child-Pugh Class A) hepatic impairment (total bilirubin ranging from 0.6 to 2 mg/dL) to 8 subjects with normal hepatic function following a single dose of 60 mg raloxifene HCl. Apparent clearance of raloxifene was reduced 56% and the half-life of raloxifene was not altered in patients with mild hepatic impairment. Plasma raloxifene concentrations were approximately 150% higher than those in healthy volunteers and correlated with total bilirubin concentrations. The pharmacokinetics of raloxifene has not been studied in patients with moderate or severe hepatic impairment. Raloxifene should be used with caution in patients with hepatic impairment [see Warnings and Precautions (5.5) and Use in Specific Populations (8.7)].

Drug Interactions

Cholestyramine — Cholestyramine, an anion exchange resin, causes a 60% reduction in the absorption and enterohepatic cycling of raloxifene after a single dose. Although not specifically studied, it is anticipated that other anion exchange resins would have a similar effect [see Drug Interactions (7.1)].

Warfarin — In vitro, raloxifene did not interact with the binding of warfarin. The concomitant administration of EVISTA and warfarin, a coumarin derivative, has been assessed in a single-dose study. In this study, raloxifene had no effect on the pharmacokinetics of warfarin. However, a 10% decrease in prothrombin time was observed in the single-dose study. In the osteoporosis treatment trial, there were no clinically relevant effects of warfarin co-administration on plasma concentrations of raloxifene [see Drug Interactions (7.2)].

Other Highly Protein-Bound Drugs — In the osteoporosis treatment trial, there were no clinically relevant effects of co-administration of other highly protein-bound drugs (e.g., gemfibrozil) on plasma concentrations of raloxifene. In vitro, raloxifene did not interact with the binding of phenytoin, tamoxifen, or warfarin (see above) [see Drug Interactions (7.3)].

Ampicillin and Amoxicillin — Peak concentrations of raloxifene and the overall extent of absorption are reduced 28% and 14%, respectively, with co-administration of ampicillin. These reductions are consistent with decreased enterohepatic cycling associated with antibiotic reduction of enteric bacteria. However, the systemic exposure and the elimination rate of raloxifene were not affected. In the osteoporosis treatment trial, co-administration of amoxicillin had no discernible differences in plasma raloxifene concentrations [see Drug Interactions (7.5)].

Antacids — Concomitant administration of calcium carbonate or aluminum and magnesium hydroxide-containing antacids does not affect the systemic exposure of raloxifene [see Drug Interactions (7.5)].

Corticosteroids — The chronic administration of raloxifene in postmenopausal women has no effect on the pharmacokinetics of methylprednisolone given as a single oral dose [see Drug Interactions (7.5)].

Digoxin — Raloxifene has no effect on the pharmacokinetics of digoxin [see Drug Interactions (7.5)].

Cyclosporine — Concomitant administration of EVISTA with cyclosporine has not been studied.

Lipid-Lowering Agents — Concomitant administration of EVISTA with lipid-lowering agents has not been studied.

13 NONCLINICAL TOXICOLOGY

13.1 Carcinogenesis, Mutagenesis, Impairment of Fertility

Carcinogenesis — In a 21-month carcinogenicity study in mice, there was an increased incidence of ovarian tumors in female animals given 9 to 242 mg/kg, which included benign and malignant tumors of granulosa/theca cell origin and benign tumors of epithelial cell origin. Systemic exposure (AUC) of raloxifene in this group was 0.3 to 34 times that in postmenopausal women administered a 60 mg dose. There was also an increased incidence of testicular interstitial cell tumors and prostatic adenomas and adenocarcinomas in male mice given 41 or 210 mg/kg (4.7 or 24 times the AUC in humans) and prostatic leiomyoblastoma in male mice given 210 mg/kg.

In a 2-year carcinogenicity study in rats, an increased incidence in ovarian tumors of granulosa/theca cell origin was observed in female rats given 279 mg/kg (approximately 400 times the AUC in humans). The female rodents in these studies were treated during their reproductive lives when their ovaries were functional and responsive to hormonal stimulation.

Mutagenesis — Raloxifene HCl was not genotoxic in any of the following test systems: the Ames test for bacterial mutagenesis with and without metabolic activation, the unscheduled DNA synthesis assay in rat hepatocytes, the mouse lymphoma assay for mammalian cell mutation, the chromosomal aberration assay in Chinese hamster ovary cells, the in vivo sister chromatid exchange assay in Chinese hamsters, and the in vivo micronucleus test in mice.

Impairment of Fertility — When male and female rats were given daily doses ≥5 mg/kg (≥0.8 times the human dose based on surface area, mg/m^2) prior to and during mating, no pregnancies occurred. In male rats, daily doses up to 100 mg/kg (16 times the human dose based on surface area, mg/m^2) for at least 2 weeks did not affect sperm production or quality or reproductive performance. In female rats, at doses of 0.1 to 10 mg/kg/day (0.02 to 1.6 times the human dose based on surface area, mg/m^2), raloxifene disrupted estrous cycles and inhibited ovulation. These effects of raloxifene were reversible. In another study in rats in which raloxifene was given during the preimplantation period at doses ≥0.1 mg/kg (≥0.02 times the human dose based on surface area, mg/m^2), raloxifene delayed and disrupted embryo implantation, resulting in prolonged gestation and reduced litter size. The reproductive and developmental effects observed in animals are consistent with the estrogen receptor activity of raloxifene.

13.2 Animal Toxicology and/or Pharmacology

The skeletal effects of raloxifene treatment were assessed in ovariectomized rats and monkeys. In rats, raloxifene prevented increased bone resorption and bone loss after ovariectomy. There were positive effects of raloxifene on bone strength, but the effects varied with time. Cynomolgus monkeys were treated with raloxifene or conjugated estrogens for 2 years. In terms of bone cycles, this is equivalent to approximately 6 years in humans. Raloxifene and estrogen suppressed bone turnover and increased BMD in the lumbar spine and in the central cancellous bone of the proximal tibia. In this animal model, there was a positive correlation between vertebral compressive breaking force and BMD of the lumbar spine.

Histologic examination of bone from rats and monkeys treated with raloxifene showed no evidence of woven bone, marrow fibrosis, or mineralization defects.

These results are consistent with data from human studies of radiocalcium kinetics and markers of bone metabolism, and are consistent with the action of EVISTA as a skeletal antiresorptive agent.

14 CLINICAL STUDIES

14.1 Treatment of Postmenopausal Osteoporosis

Effect on Fracture Incidence

The effects of EVISTA on fracture incidence and BMD in postmenopausal women with osteoporosis were examined at 3 years in a large randomized, placebo-controlled, double-blind, multinational osteoporosis treatment trial (MORE). All vertebral fractures were diagnosed radiographically; some of these fractures also were associated with symptoms (i.e., clinical fractures). The study population consisted of 7705 postmenopausal women with osteoporosis as defined by: a) low BMD (vertebral or hip BMD at least 2.5 standard deviations below the mean value for healthy young women) without baseline vertebral fractures or b) one or more baseline vertebral fractures. Women enrolled in this study had a median age of 67 years (range 31 to 80) and a median time since menopause of 19 years.

Effect on Bone Mineral Density

EVISTA, 60 mg administered once daily, increased spine and hip BMD by 2 to 3%. EVISTA decreased the incidence of the first vertebral fracture from 4.3% for placebo to 1.9% for EVISTA (relative risk reduction = 55%) and subsequent vertebral fractures from 20.2% for placebo to 14.1% for EVISTA (relative risk reduction = 30%) (see Table 4). All women in the study received calcium (500 mg/day) and vitamin D (400 to 600 IU/day). EVISTA reduced the incidence of vertebral fractures whether or not patients had a vertebral fracture upon study entry. The decrease in incidence of vertebral fracture was greater than could be accounted for by increase in BMD alone.

Table 4: Effect of EVISTA on Risk of Vertebral Fractures
 | Number of Patients |  | Absolute Risk Reduction (ARR) | Relative Risk Reduction (95% CI)
 | EVISTA | Placebo
Fractures diagnosed radiographically
Patients with no baseline fracturea | n=1401 | n=1457
Number (%) of patients with ≥1 new vertebral fracture | 27 (1.9%) | 62 (4.3%) | 2.4% | 55% (29%, 71%)
Patients with ≥1 baseline fracturea | n=858 | n=835
Number (%) of patients with ≥1 new vertebral fracture | 121 (14.1%) | 169 (20.2%) | 6.1% | 30% (14%, 44%)
Symptomatic vertebral fractures
All randomized patients | n=2557 | n=2576
Number (%) of patients with ≥1 new clinical (painful) vertebral fracture | 47 (1.8%) | 81 (3.1%) | 1.3% | 41% (17%, 59%)
a Includes all patients with baseline and at least one follow-up radiograph.

The mean percentage change in BMD from baseline for EVISTA was statistically significantly greater than for placebo at each skeletal site (see Table 5).

Table 5: EVISTA- (60 mg Once Daily) Related Increases in BMDa for the Osteoporosis Treatment Study Expressed as Mean Percentage Increase vs. Placebob, c
Site | Time
Site | 12 Months % | 24 Months % | 36 Months %
Lumbar Spine | 2.0 | 2.6 | 2.6
Femoral Neck | 1.3 | 1.9 | 2.1
Ultradistal Radius | NDd | 2.2 | NDd
Distal Radius | NDd | 0.9 | NDd
Total Body | NDd | 1.1 | NDd
a Note: all BMD increases were significant (p<0.001).
b Intent-to-treat analysis; last observation carried forward.
c All patients received calcium and vitamin D.
d ND = not done (total body and radius BMD were measured only at 24 months).

Discontinuation from the study was required when excessive bone loss or multiple incident vertebral fractures occurred. Such discontinuation was statistically significantly more frequent in the placebo group (3.7%) than in the EVISTA group (1.1%).

Bone Histology

Bone biopsies for qualitative and quantitative histomorphometry were obtained at baseline and after 2 years of treatment. There were 56 paired biopsies evaluable for all indices. In EVISTA-treated patients, there were statistically significant decreases in bone formation rate per tissue volume, consistent with a reduction in bone turnover. Normal bone quality was maintained; specifically, there was no evidence of osteomalacia, marrow fibrosis, cellular toxicity, or woven bone after 2 years of treatment.

Effect on Endometrium

Endometrial thickness was evaluated annually in a subset of the study population (1781 patients) for 3 years. Placebo-treated women had a 0.27 mm mean decrease from baseline in endometrial thickness over 3 years, whereas the EVISTA-treated women had a 0.06 mm mean increase. Patients in the osteoporosis treatment study were not screened at baseline or excluded for pre-existing endometrial or uterine disease. This study was not specifically designed to detect endometrial polyps. Over the 36 months of the study, clinically or histologically benign endometrial polyps were reported in 17 of 1999 placebo-treated women, 37 of 1948 EVISTA-treated women, and in 31 of 2010 women treated with raloxifene HCl 120 mg/day. There was no difference between EVISTA- and placebo-treated women in the incidences of endometrial carcinoma, vaginal bleeding, or vaginal discharge.

14.2 Prevention of Postmenopausal Osteoporosis

The effects of EVISTA on BMD in postmenopausal women were examined in three randomized, placebo-controlled, double-blind osteoporosis prevention trials: (1) a North American trial enrolled 544 women; (2) a European trial, 601 women; and (3) an international trial, 619 women who had undergone hysterectomy. In these trials, all women received calcium supplementation (400 to 600 mg/day). Women enrolled in these trials had a median age of 54 years and a median time since menopause of 5 years (less than 1 year up to 15 years postmenopause). The majority of the women were White (93.5%). Women were included if they had spine BMD between 2.5 standard deviations below and 2 standard deviations above the mean value for healthy young women. The mean T scores (number of standard deviations above or below the mean in healthy young women) for the three trials ranged from -1.01 to -0.74 for spine BMD and included women both with normal and low BMD. EVISTA, 60 mg administered once daily, produced increases in bone mass versus calcium supplementation alone, as reflected by dual-energy x-ray absorptiometric (DXA) measurements of hip, spine, and total body BMD.

Effect on Bone Mineral Density

Compared with placebo, the increases in BMD for each of the three studies were statistically significant at 12 months and were maintained at 24 months (see Table 6). The placebo groups lost approximately 1% of BMD over 24 months.

Table 6: EVISTA- (60 mg Once Daily) Related Increases in BMDa for the Three Osteoporosis Prevention Studies Expressed as Mean Percentage Increase vs. Placebob at 24 Monthsc
Site | Study
Site | NAd % | EUd % | INTd, e %
Total Hip | 2.0 | 2.4 | 1.3
Femoral Neck | 2.1 | 2.5 | 1.6
Trochanter | 2.2 | 2.7 | 1.3
Intertrochanter | 2.3 | 2.4 | 1.3
Lumbar Spine | 2.0 | 2.4 | 1.8
a Note: all BMD increases were significant (p≤0.001).
b All patients received calcium.
c Intent-to-treat analysis; last observation carried forward.
d Abbreviations: NA = North American, EU = European, INT = International.
e All women in the study had previously undergone hysterectomy.

EVISTA also increased BMD compared with placebo in the total body by 1.3% to 2.0% and in Ward's Triangle (hip) by 3.1% to 4.0%. The effects of EVISTA on forearm BMD were inconsistent between studies. In Study EU, EVISTA prevented bone loss at the ultradistal radius, whereas in Study NA, it did not (see Figure 1).

Figure 1: Total hip bone mineral density mean percentage change from baseline

Effect on Endometrium

In placebo-controlled osteoporosis prevention trials, endometrial thickness was evaluated every 6 months (for 24 months) by transvaginal ultrasonography (TVU). A total of 2978 TVU measurements were collected from 831 women in all dose groups. Placebo-treated women had a 0.04 mm mean increase from baseline in endometrial thickness over 2 years, whereas the EVISTA-treated women had a 0.09 mm mean increase. Endometrial thickness measurements in raloxifene-treated women were indistinguishable from placebo. There were no differences between the raloxifene and placebo groups with respect to the incidence of reported vaginal bleeding.

14.3 Reduction in Risk of Invasive Breast Cancer in Postmenopausal Women with Osteoporosis

MORE Trial

The effect of EVISTA on the incidence of breast cancer was assessed as a secondary safety endpoint in a randomized, placebo-controlled, double-blind, multinational osteoporosis treatment trial in postmenopausal women [see Clinical Studies (14.1)]. After 4 years, EVISTA, 60 mg administered once daily, reduced the incidence of all breast cancers by 62%, compared with placebo (HR 0.38, 95% CI 0.22-0.67). EVISTA reduced the incidence of invasive breast cancer by 71%, compared with placebo (ARR 3.1 per 1000 women-years); this was primarily due to an 80% reduction in the incidence of ER-positive invasive breast cancer in the EVISTA group compared with placebo. Table 7 presents efficacy and selected safety outcomes.

CORE Trial

The effect of EVISTA on the incidence of invasive breast cancer was evaluated for 4 additional years in a follow-up study conducted in a subset of postmenopausal women originally enrolled in the MORE osteoporosis treatment trial. Women were not re-randomized; the treatment assignment from the osteoporosis treatment trial was carried forward to this study. EVISTA, 60 mg administered once daily, reduced the incidence of invasive breast cancer by 56%, compared with placebo (ARR 3.0 per 1000 women-years); this was primarily due to a 63% reduction in the incidence of ER-positive invasive breast cancer in the EVISTA group compared with placebo. There was no reduction in the incidence of ER-negative breast cancer. In the osteoporosis treatment trial and the follow-up study, there was no difference in incidence of noninvasive breast cancer between the EVISTA and placebo groups. Table 7 presents efficacy and selected safety outcomes.

In a subset of postmenopausal women followed for up to 8 years from randomization in MORE to the end of CORE, EVISTA, 60 mg administered once daily, reduced the incidence of invasive breast cancer by 60% in women assigned EVISTA (N=1355) compared with placebo (N=1286) (HR 0.40, 95% CI 0.21, 0.77; ARR 1.95 per 1000 women-years); this was primarily due to a 65% reduction in the incidence of ER-positive invasive breast cancer in the EVISTA group compared with placebo.

Table 7: EVISTA (60 mg Once Daily) vs. Placebo on Outcomes in Postmenopausal Women with Osteoporosis
Outcomes | MORE 4 years |  |  |  |  | COREa 4 years
Outcomes | Placebo (N=2576) |  | EVISTA (N=2557) |  | HR (95% CI)b | Placebo (N=1286) |  | EVISTA (N=2725) |  | HR (95% CI)b
Outcomes | n | IRb | n | IRb |  | n | IRb | n | IRb
Invasivec breast cancer | 38 | 4.36 | 11 | 1.26 | 0.29 (0.15, 0.56)d | 20 | 5.41 | 19 | 2.43 | 0.44 (0.24, 0.83)d
ERb, c positive | 29 | 3.33 | 6 | 0.69 | 0.20 (0.08, 0.49) | 15 | 4.05 | 12 | 1.54 | 0.37 (0.17, 0.79)
ERb, c negative | 4 | 0.46 | 5 | 0.57 | 1.23 (0.33, 4.60) | 3 | 0.81 | 6 | 0.77 | 0.95 (0.24, 3.79)
ERb, c unknown | 5 | 0.57 | 0 | 0.00 | N/Ab | 2 | 0.54 | 1 | 0.13 | N/Ab
Noninvasivec, e breast cancer | 5 | 0.57 | 3 | 0.34 | 0.59 (0.14, 2.47) | 2 | 0.54 | 5 | 0.64 | 1.18 (0.23, 6.07)
Clinical vertebral fractures | 107 | 12.27 | 62 | 7.08 | 0.57 (0.42, 0.78) | N/Ab | N/Ab | N/Ab | N/Ab | N/Ab
Death | 36 | 4.13 | 23 | 2.63 | 0.63 (0.38, 1.07) | 29 | 7.76 | 47 | 5.99 | 0.77 (0.49, 1.23)
Death due to stroke | 6 | 0.69 | 3 | 0.34 | 0.49 (0.12, 1.98) | 1 | 0.27 | 6 | 0.76 | 2.87 (0.35, 23.80)
Stroke | 56 | 6.42 | 43 | 4.91 | 0.76 (0.51, 1.14) | 14 | 3.75 | 49 | 6.24 | 1.67 (0.92, 3.03)
Deep vein thrombosis | 8 | 0.92 | 20 | 2.28 | 2.50 (1.10, 5.68) | 4 | 1.07 | 17 | 2.17 | 2.03 (0.68, 6.03)
Pulmonary embolism | 4 | 0.46 | 11 | 1.26 | 2.76 (0.88, 8.67) | 0 | 0.00 | 9 | 1.15 | N/Ab
Endometrial and uterine cancerf | 5 | 0.74 | 5 | 0.74 | 1.01 (0.29, 3.49) | 3 | 1.02 | 4 | 0.65 | 0.64 (0.14, 2.85)
Ovarian cancer | 6 | 0.69 | 3 | 0.34 | 0.49 (0.12, 1.95) | 2 | 0.54 | 2 | 0.25 | 0.47 (0.07, 3.36)
Hot flashes | 151 | 17.31 | 237 | 27.06 | 1.61 (1.31, 1.97) | 11 | 2.94 | 26 | 3.31 | 1.12 (0.55, 2.27)
Peripheral edema | 134 | 15.36 | 164 | 18.73 | 1.23 (0.98, 1.54) | 30 | 8.03 | 61 | 7.77 | 0.96 (0.62, 1.49)
Cholelithiasis | 45 | 5.16 | 53 | 6.05 | 1.18 (0.79, 1.75) | 12 | 3.21 | 35 | 4.46 | 1.39 (0.72, 2.67)
a CORE was a follow-up study conducted in a subset of 4011 postmenopausal women who originally enrolled in MORE. Women were not re-randomized; the treatment assignment from MORE was carried forward to this study. At CORE enrollment, the EVISTA group included 2725 total patients with 1355 patients who were originally assigned to raloxifene HCl 60 mg once daily and 1370 patients who were originally assigned to raloxifene HCl 120 mg at MORE randomization.
b Abbreviations: CI = confidence interval; ER = estrogen receptor; HR = hazard ratio; IR = annual incidence rate per 1000 women; N/A = not applicable.
c Included 1274 patients in placebo and 2716 patients in EVISTA who were not diagnosed with breast cancer prior to CORE enrollment.
d p<0.05, obtained from the log-rank test, and not adjusted for multiple comparisons in MORE.
e All cases were ductal carcinoma in situ.
f Only patients with an intact uterus were included (MORE: placebo = 1999, EVISTA = 1950; CORE: placebo = 1008, EVISTA = 2138).

RUTH Trial

The effect of EVISTA on the incidence of invasive breast cancer was assessed in a randomized, placebo-controlled, double-blind, multinational study in 10,101 postmenopausal women at increased risk of coronary events. Women in this study had a median age of 67.6 years (range 55-92) and were followed for a median of 5.6 years (range 0.01-7.1). Eighty-four percent were White, 9.8% of women reported a first-degree relative with a history of breast cancer, and 41.4% of the women had a 5-year predicted risk of invasive breast cancer ≥1.66%, based on the modified Gail model.

EVISTA, 60 mg administered once daily, reduced the incidence of invasive breast cancer by 44% compared with placebo [absolute risk reduction (ARR) 1.2 per 1000 women-years]; this was primarily due to a 55% reduction in estrogen receptor (ER)-positive invasive breast cancer in the EVISTA group compared with placebo (ARR 1.2 per 1000 women-years). There was no reduction in ER-negative invasive breast cancer. Table 8 presents efficacy and selected safety outcomes.

Table 8: EVISTA (60 mg Once Daily) vs. Placebo on Outcomes in Postmenopausal Women at Increased Risk for Major Coronary Events
Outcomes | Placeboa (N=5057) |  | EVISTAa (N=5044) |  | HR (95% CI)b
Outcomes | n | IRb | n | IRb
Invasive breast cancer | 70 | 2.66 | 40 | 1.50 | 0.56 (0.38, 0.83)c
ERb positive | 55 | 2.09 | 25 | 0.94 | 0.45 (0.28, 0.72)
ERb negative | 9 | 0.34 | 13 | 0.49 | 1.44 (0.61, 3.36)
ERb unknown | 6 | 0.23 | 2 | 0.07 | 0.33 (0.07, 1.63)
Noninvasived breast cancer | 5 | 0.19 | 11 | 0.41 | 2.17 (0.75, 6.24)
Clinical vertebral fractures | 97 | 3.70 | 64 | 2.40 | 0.65 (0.47, 0.89)
Death | 595 | 22.45 | 554 | 20.68 | 0.92 (0.82, 1.03)
Death due to stroke | 39 | 1.47 | 59 | 2.20 | 1.49 (1.00, 2.24)
Stroke | 224 | 8.60 | 249 | 9.46 | 1.10 (0.92, 1.32)
Deep vein thrombosis | 47 | 1.78 | 65 | 2.44 | 1.37 (0.94, 1.99)
Pulmonary embolism | 24 | 0.91 | 36 | 1.35 | 1.49 (0.89, 2.49)
Endometrial and uterine cancere | 17 | 0.83 | 21 | 1.01 | 1.21 (0.64 - 2.30)
Ovarian cancerf | 10 | 0.41 | 17 | 0.70 | 1.69 (0.78, 3.70)
Hot flashes | 241 | 9.09 | 397 | 14.82 | 1.68 (1.43, 1.97)
Peripheral edema | 583 | 22.00 | 706 | 26.36 | 1.22 (1.09, 1.36)
Cholelithiasisg | 131 | 6.20 | 168 | 7.83 | 1.26 (1.01, 1.59)
a Note: There were a total of 76 breast cancer cases in the placebo group and 52 in the EVISTA group. For two cases, one in each treatment group, invasive status was unknown.
b Abbreviations: CI = confidence interval; ER = estrogen receptor; HR = hazard ratio; IR = annual incidence rate per 1000 women.
c p<0.05, obtained from the log-rank test, after adjusting for the co-primary endpoint of major coronary events.
d All cases were ductal carcinoma in situ.
e Only patients with an intact uterus were included (placebo = 3882, EVISTA = 3900).
f Only patients with at least one ovary were included (placebo = 4606, EVISTA = 4559).
g Only patients with an intact gallbladder at baseline were included (placebo = 4111, EVISTA = 4144).

The effect of EVISTA in reducing the incidence of invasive breast cancer was consistent among women above or below age 65 or with a 5-year predicted invasive breast cancer risk, based on the modified Gail model, <1.66%, or ≥1.66%.

14.4 Reduction in Risk of Invasive Breast Cancer in Postmenopausal Women at High Risk of Invasive Breast Cancer

STAR Trial

The effects of EVISTA 60 mg/day versus tamoxifen 20 mg/day over 5 years on reducing the incidence of invasive breast cancer were assessed in 19,747 postmenopausal women in a randomized, double-blind trial conducted in North America by the National Surgical Adjuvant Breast and Bowel Project and sponsored by the National Cancer Institute. Women in this study had a mean age of 58.5 years (range 35-83), a mean 5-year predicted invasive breast cancer risk of 4.03% (range 1.66-23.61%), and 9.1% had a history of lobular carcinoma in situ (LCIS). More than 93% of participants were White. As of 31 December 2005, the median time of follow-up was 4.3 years (range 0.07-6.50 years).

EVISTA was not superior to tamoxifen in reducing the incidence of invasive breast cancer. The observed incidence rates of invasive breast cancer were EVISTA 4.4 and tamoxifen 4.3 per 1000 women per year. The results from a noninferiority analysis are consistent with EVISTA potentially losing up to 35% of the tamoxifen effect on reduction of invasive breast cancer. The effect of each treatment on invasive breast cancer was consistent when women were compared by baseline age, history of LCIS, history of atypical hyperplasia, 5-year predicted risk of breast cancer by the modified Gail model, or the number of relatives with a history of breast cancer. Fewer noninvasive breast cancers occurred in the tamoxifen group compared to the EVISTA group. Table 9 presents efficacy and selected safety outcomes.

Table 9: EVISTA (60 mg Once Daily) vs. Tamoxifen (20 mg Once Daily) on Outcomes in Postmenopausal Women at Increased Risk for Invasive Breast Cancer
Outcomes | EVISTA (N=9751) |  | Tamoxifen (N=9736) |  | RR (95% CI)a
Outcomes | n | IRa | n | IRa
Invasive breast cancer | 173 | 4.40 | 168 | 4.30 | 1.02 (0.82, 1.27)
ERa positive | 115 | 2.93 | 120 | 3.07 | 0.95 (0.73, 1.24)
ERa negative | 52 | 1.32 | 46 | 1.18 | 1.12 (0.74, 1.71)
ERa unknown | 6 | 0.15 | 2 | 0.05 | 2.98 (0.53, 30.21)
Noninvasive breast cancerb | 83 | 2.12 | 60 | 1.54 | 1.38 (0.98, 1.95)
DCISa | 47 | 1.20 | 32 | 0.82 | 1.46 (0.91, 2.37)
LCISa | 29 | 0.74 | 23 | 0.59 | 1.26 (0.70, 2.27)
Uterine cancerc | 23 | 1.21 | 37 | 1.99 | 0.61 (0.34, 1.05)
Endometrial hyperplasiac | 17 | 0.90 | 100 | 5.42 | 0.17 (0.09, 0.28)
Hysterectomyc | 92 | 4.84 | 246 | 13.25 | 0.37 (0.28, 0.47)
Ovarian cancerd | 18 | 0.66 | 14 | 0.52 | 1.27 (0.60, 2.76)
Ischemic heart diseasee | 138 | 3.50 | 125 | 3.19 | 1.10 (0.86, 1.41)
Stroke | 54 | 1.36 | 56 | 1.42 | 0.96 (0.65, 1.42)
Deep vein thrombosis | 67 | 1.69 | 92 | 2.35 | 0.72 (0.52, 1.00)
Pulmonary embolism | 38 | 0.96 | 58 | 1.47 | 0.65 (0.42, 1.00)
Clinical vertebral fractures | 58 | 1.46 | 58 | 1.47 | 0.99 (0.68, 1.46)
Cataractsf | 343 | 10.34 | 435 | 13.19 | 0.78 (0.68, 0.91)
Cataract surgeryf | 240 | 7.17 | 295 | 8.85 | 0.81 (0.68, 0.96)
Death | 104 | 2.62 | 109 | 2.76 | 0.95 (0.72, 1.25)
Edemag | 741 | 18.66 | 664 | 16.83 | 1.11 (1.00, 1.23)
Hot flashes | 6748 | 169.91 | 7170 | 181.71 | 0.94 (0.90, 0.97)
a Abbreviations: CI = confidence interval; DCIS = ductal carcinoma in situ; ER = estrogen receptor; IR = annual incidence rate per 1000 women; LCIS = lobular carcinoma in situ; RR = risk ratio for women in the EVISTA group compared with those in the tamoxifen group.
b Of the 60 noninvasive breast cases in the tamoxifen group, 5 were mixed types. Of the 83 noninvasive breast cancers in the raloxifene group, 7 were mixed types.
c Only patients with an intact uterus at baseline were included (tamoxifen = 4739, EVISTA = 4715).
d Only patients with at least one intact ovary at baseline were included (tamoxifen = 6813, EVISTA = 6787).
e Defined as myocardial infarction, severe angina, or acute ischemic syndromes.
f Only patients who were free of cataracts at baseline were included (tamoxifen = 8342, EVISTA = 8333).
g Peripheral edema events are included in the term edema.

14.5 Effects on Cardiovascular Disease

In a randomized, placebo-controlled, double-blind, multinational clinical trial (RUTH) of 10,101 postmenopausal women with documented coronary heart disease or at increased risk for coronary events, no cardiovascular benefit was demonstrated after treatment with EVISTA 60 mg once daily for a median follow-up of 5.6 years. No significant increase or decrease was observed for coronary events (death from coronary causes, nonfatal myocardial infarction, or hospitalization for an acute coronary syndrome). An increased risk of death due to stroke after treatment with EVISTA was observed: 59 (1.2%) EVISTA-treated women died due to a stroke compared to 39 (0.8%) placebo-treated women (2.2 versus 1.5 per 1000 women-years; hazard ratio 1.49; 95% confidence interval, 1.00-2.24; p=0.0499). The incidence of stroke did not differ significantly between treatment groups (249 with EVISTA [4.9%] versus 224 with placebo [4.4%]; hazard ratio 1.10; 95% confidence interval 0.92-1.32; p=0.30; 9.5 versus 8.6 per 1000 women-years) [see Warnings and Precautions (5.2, 5.3)].

16 HOW SUPPLIED/STORAGE AND HANDLING

16.1 How Supplied

EVISTA 60 mg tablets are white, elliptical, film coated (not scored) and imprinted with 4165 on one side in edible blue ink. They are available as follows:

Presentation and NDC
Bottles of 30 (unit of use) | 0002-4184-30

16.2 Storage and Handling

Store at controlled room temperature, 20° to 25°C (68° to 77°F) [see USP]. The USP defines controlled room temperature as a temperature maintained thermostatically that encompasses the usual and customary working environment of 20° to 25°C (68° to 77°F); that results in a mean kinetic temperature calculated to be not more than 25°C; and that allows for excursions between 15° and 30°C (59° and 86°F) that are experienced in pharmacies, hospitals, and warehouses.

17 PATIENT COUNSELING INFORMATION

See FDA-approved Medication Guide.

Physicians should instruct their patients to read the Medication Guide before starting therapy with EVISTA and to reread it each time the prescription is renewed.

17.1 Osteoporosis Recommendations, Including Calcium and Vitamin D Supplementation

For osteoporosis treatment or prevention, patients should be instructed to take supplemental calcium and/or vitamin D if intake is inadequate. Patients at increased risk for vitamin D insufficiency (e.g., over the age of 70 years, nursing home bound, chronically ill, or with gastrointestinal malabsorption syndromes) should be instructed to take additional vitamin D if needed. Weight-bearing exercises should be considered along with the modification of certain behavioral factors, such as cigarette smoking and/or excessive alcohol consumption, if these factors exist.

17.2 Patient Immobilization

EVISTA should be discontinued at least 72 hours prior to and during prolonged immobilization (e.g., post-surgical recovery, prolonged bed rest), and patients should be advised to avoid prolonged restrictions of movement during travel because of the increased risk of venous thromboembolic events [see Warnings and Precautions (5.1)].

17.3 Hot Flashes or Flushes

EVISTA may increase the incidence of hot flashes and is not effective in reducing hot flashes or flushes associated with estrogen deficiency. In some asymptomatic patients, hot flashes may occur upon beginning EVISTA therapy.

17.4 Reduction in Risk of Invasive Breast Cancer in Postmenopausal Women with Osteoporosis or at High Risk of Invasive Breast Cancer

Use of EVISTA is associated with the reduction of the risk of invasive breast cancer in postmenopausal women. EVISTA has not been shown to reduce the risk of noninvasive breast cancer. When considering treatment, physicians need to discuss the potential benefits and risks of EVISTA treatment with the patient.

EVISTA is not indicated for the treatment of invasive breast cancer or reduction of the risk of recurrence.

Patients should have breast exams and mammograms before starting EVISTA and should continue regular breast exams and mammograms in keeping with good medical practice after beginning treatment with EVISTA.

Marketed by: Lilly USA, LLC
Indianapolis, IN 46285, USA

Copyright © 1997, 2023, Eli Lilly and Company. All rights reserved.

EVS-0005-USPI-20230306

Medication Guide

EVISTA® (Ē-VISS-tah)

(raloxifene hydrochloride tablets)
Tablets for Oral Use

Read the Medication Guide that comes with EVISTA before you start taking it and each time you refill your prescription. The information may have changed. This Medication Guide does not take the place of talking with your doctor about your medical condition or treatment. Talk with your doctor about EVISTA when you start taking it and at regular checkups.

What is the most important information I should know about EVISTA?

Serious and life-threatening side effects can occur while taking EVISTA. These include blood clots and dying from stroke:

- Increased risk of blood clots in the legs (deep vein thrombosis) and lungs (pulmonary embolism) have been reported with EVISTA. Women who have or have had blood clots in the legs, lungs, or eyes should not take EVISTA.
- Women who have had a heart attack or are at risk for a heart attack may have an increased risk of dying from stroke when taking EVISTA.

1. Before starting EVISTA, tell your doctor if you have had blood clots in your legs, lungs, or eyes, a stroke, mini-stroke (transient ischemic attack), or have an irregular heartbeat.
2. Stop taking EVISTA and call your doctor if you have:
  - leg pain or a feeling of warmth in the lower leg (calf).
  - swelling of the legs, hands, or feet.
  - sudden chest pain, shortness of breath, or coughing up blood.
  - sudden change in your vision, such as loss of vision or blurred vision.
3. Being still for a long time (such as sitting still during a long car or airplane trip or being in bed after surgery) can increase your risk of blood clots. (See “What should I avoid if I am taking EVISTA?”)

What is EVISTA?

EVISTA is a type of prescription medicine called a Selective Estrogen Receptor Modulator (SERM). EVISTA is for women after menopause, and has more than one use:

- Osteoporosis: EVISTA treats and prevents osteoporosis by helping make your bones stronger and less likely to break.
- Invasive Breast Cancer: If you have osteoporosis or are at high risk for breast cancer, EVISTA can be used to lower your chance of getting invasive breast cancer. EVISTA will not totally get rid of your chance of getting breast cancer. Your doctor can estimate your risk of breast cancer by asking you about risk factors, including:
  - your age (getting older).
  - family history of breast cancer in your mother, sister, or daughter.
  - a history of any breast biopsy, especially an abnormal biopsy.
  You and your doctor should talk about whether the possible benefit of EVISTA in lowering your chance of getting invasive breast cancer is greater than its possible risks.

EVISTA is not for use in premenopausal women (women who have not passed menopause).

Who should not take EVISTA?

Do not take EVISTA if you:

- have or have had blood clots in your legs, lungs, or eyes. Taking EVISTA may increase the risk of getting blood clots.
- are pregnant or could become pregnant. EVISTA could harm your unborn child.
- are nursing a baby. It is not known if EVISTA passes into breast milk or what effect it might have on the baby.

What should I tell my doctor before taking EVISTA?

EVISTA may not be right for you. Before taking EVISTA, tell your doctor about all your medical conditions, including if you:

- have had blood clots in your legs, lungs, or eyes, a stroke, mini-stroke (TIA/transient ischemic attack), or a type of irregular heartbeat (atrial fibrillation).
- have had breast cancer. EVISTA has not been fully studied in women who have a history of breast cancer.
- have liver or kidney problems.
- have taken estrogen in the past and had a high increase of triglycerides (a kind of fat in the blood).
- are pregnant, planning to become pregnant, or breast-feeding (see “Who should not take EVISTA?”).

Tell your doctor about all medicines you take, including prescription and non-prescription medicines, vitamins, and herbal supplements. Know the medicines you take. Keep a list of them and show it to your doctor and pharmacist each time you get a new medicine. Especially tell your doctor if you take*:

- warfarin (Coumadin®, Jantoven®)
  If you are taking warfarin or other coumarin blood thinners, your doctor may need to do a blood test when you first start or if you need to stop taking EVISTA. Names for this test include “prothrombin time,” “pro-time,” or “INR.” Your doctor may need to adjust the dose of your warfarin or other coumarin blood thinner.
- cholestyramine
- estrogens

EVISTA should not be taken with cholestyramine or estrogens.

How should I take EVISTA?

- Take EVISTA exactly how your doctor tells you to.
- Keep taking EVISTA for as long as your doctor prescribes it for you. It is not known how long you should keep taking EVISTA to lower your chance of getting invasive breast cancers.
- It is important to get your refills on time so you do not run out of the medicine.
- Take one EVISTA tablet each day.
- Take EVISTA at any time of the day, with or without food.
- To help you remember to take EVISTA, it may be best to take it at about the same time each day.
- Calcium and vitamin D may be taken at the same time as EVISTA. It is important to take calcium and vitamin D, as directed by your physician, to prevent or treat osteoporosis.
- If you miss a dose, take it as soon as you remember. However, if it is almost time for your next dose, skip the missed dose and take only your next regularly scheduled dose. Do not take two doses at the same time.

What should I avoid while taking EVISTA?

- Being still for a long time (such as during long trips or being in bed after surgery) can increase the risk of blood clots. EVISTA may add to this risk. If you will need to be still for a long time, talk with your doctor about ways to reduce the risk of blood clots. On long trips, move around periodically. Stop taking EVISTA at least 3 days before a planned surgery or before you plan on being still for a long time. You should start taking EVISTA again when you return to your normal activities.
- Some medicines should not be taken with EVISTA (see “What should I tell my doctor before taking EVISTA?”).

What are the possible side effects of EVISTA?

Serious and life-threatening side effects can occur while taking EVISTA. These include blood clots and dying from stroke:

- Increased risk of blood clots in the legs (deep vein thrombosis) and lungs (pulmonary embolism) have been reported with EVISTA. Women who have or have had blood clots in the legs, lungs, or eyes should not take EVISTA.
- Women who have had a heart attack or are at risk for a heart attack may have an increased risk of dying from stroke when taking EVISTA.

See “What is the most important information I should know about EVISTA?”

The most common side effects of EVISTA are hot flashes, leg cramps, swelling of the feet, ankles, and legs, flu syndrome, joint pain, and sweating. Hot flashes are more common during the first 6 months after starting treatment.

These are not all the side effects of EVISTA. Tell your doctor about any side effect that bothers you or that does not go away. Call your doctor for medical advice about side effects. You may report side effects to FDA at 1-800-FDA-1088.

What else should I know about EVISTA?

- Do not use EVISTA to prevent heart disease, heart attack, or strokes.
- To get the calcium and vitamin D you need, your doctor may advise you to change your diet and/or take supplemental calcium and vitamin D. Your doctor may suggest other ways to help treat or prevent osteoporosis, in addition to taking EVISTA and getting the calcium and vitamin D you need. These may include regular exercise, stopping smoking, and drinking less alcohol.
- Women who have hot flashes can take EVISTA. EVISTA does not treat hot flashes, and it may cause hot flashes in some women. (See “What are the possible side effects of EVISTA?”)
- EVISTA has not been found to cause breast tenderness or enlargement. If you notice any changes in your breasts, call your doctor to find out the cause. Before starting and while taking EVISTA you should have breast exams and mammograms, as directed by your doctor. Because EVISTA does not eliminate the chance of developing breast cancers, you need these examinations to find any breast cancers as early as possible.
- EVISTA should not cause spotting or menstrual-type bleeding. If you have any vaginal bleeding, call your doctor to find out the cause. EVISTA has not been found to increase the risk for cancer of the lining of the uterus.
- Women in clinical trials have taken EVISTA for up to eight years.

How should I store EVISTA?

- Store EVISTA at 68°F to 77°F (20°C-25°C).
- Keep EVISTA and all medicines out of the reach of children.

General Information about the safe and effective use of EVISTA

Medicines are sometimes prescribed for purposes other than those listed in a Medication Guide. Do not use EVISTA for a condition for which it was not prescribed. Do not give your EVISTA to other people, even if they have the same symptoms you have. It may harm them.

This Medication Guide is a summary of the most important information about EVISTA. If you would like more information about EVISTA, talk with your doctor. You can ask your doctor or pharmacist for information about EVISTA that is written for health professionals. For more information, call 1-800-545-5979 (toll-free).

What are the ingredients in EVISTA?

Active Ingredient: raloxifene hydrochloride

Inactive Ingredients: anhydrous lactose, carnauba wax, crospovidone, FD&C Blue No. 2 aluminum lake, hypromellose, lactose monohydrate, magnesium stearate, modified pharmaceutical glaze, polyethylene glycol, polysorbate 80, povidone, propylene glycol, and titanium dioxide.

This Medication Guide has been approved by the U.S. Food and Drug Administration.

*The brands listed are trademarks of their respective owners and are not trademarks of Eli Lilly and Company. The makers of these brands are not affiliated with and do not endorse Eli Lilly and Company or its products.

Medication Guide revised August 1, 2014

Marketed by: Lilly USA, LLC, Indianapolis, IN 46285, USA

Copyright © 1997, 2014, Eli Lilly and Company. All rights reserved.

EVS-0001-MG-20140801

PACKAGE LABEL – Evista 60mg 30ct Bottle (0002-4184)

NDC 0002-4184-30

30 Tablets

No. 4165

EVISTA®

raloxifene HCl tablets 60mg

Rx only

4165

Lilly